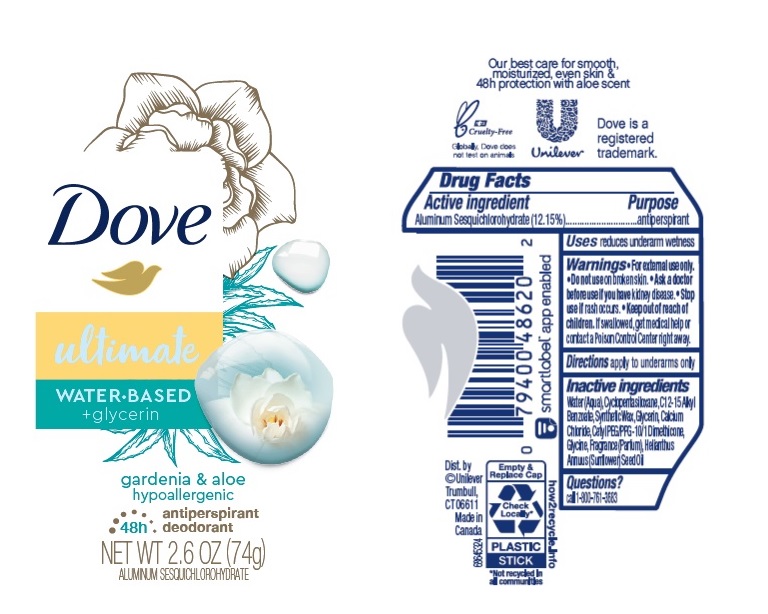 DRUG LABEL: Dove
NDC: 64942-1917 | Form: STICK
Manufacturer: Conopco Inc. d/b/a/ Unilever
Category: otc | Type: HUMAN OTC DRUG LABEL
Date: 20241024

ACTIVE INGREDIENTS: ALUMINUM SESQUICHLOROHYDRATE 12.15 g/100 g
INACTIVE INGREDIENTS: CYCLOMETHICONE 5; SUNFLOWER OIL; SYNTHETIC WAX (1200 MW); ALKYL (C12-15) BENZOATE; GLYCINE; GLYCERIN; CALCIUM CHLORIDE; CETYL PEG/PPG-10/1 DIMETHICONE (HLB 2); WATER

Dove Ultimate Gardenia & Aloe 48h Antiperspirant Deodorant

Drug Facts

Active ingredient

Aluminum Sesquichlorohydrate (12.15 %)

Purpose

antiperspirant

Uses

reduces underarm wetness

Warnings

• For external use only.
• Do not use on broken skin .
• Ask a doctor before use if you have kidney disease.
• Stop use if rash occurs.

• Keep out of reach of children.

If swallowed, get medical help or contact a Poison Control Center right away.

Directions

apply to underarms only

Inactive ingredients

Water (Aqua), Cyclopentasiloxane, C12-15 Alkyl Benzoate, Synthetic Wax, Glycerin, Calcium Chloride, Cetyl PEG/PPG-10/1 Dimethicone, Glycine, Fragrance (Parfum), Helianthus Annuus (Sunflower) Seed Oil

Questions?

Call toll-free 1-800-761-3683